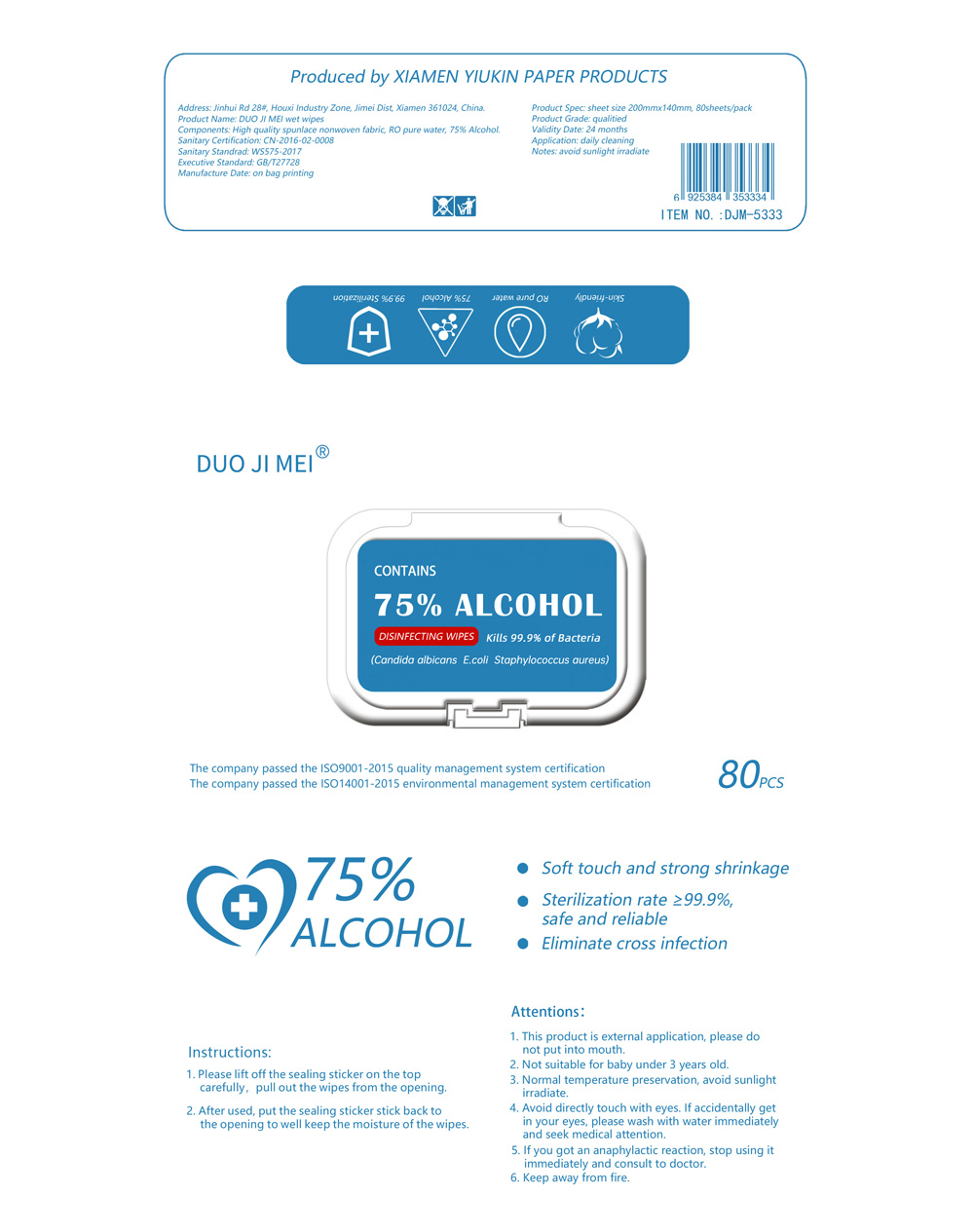 DRUG LABEL: Disinfecting Wipes
NDC: 79288-001 | Form: CLOTH
Manufacturer: Xiamen Yiukin Paper Products Co.,ltd
Category: otc | Type: HUMAN OTC DRUG LABEL
Date: 20230304

ACTIVE INGREDIENTS: ALCOHOL 75 mL/100 g
INACTIVE INGREDIENTS: WATER

Disinfecting Wipes

Active Ingredient(s)

Alcohol 75% v/v. Purpose: Antiseptic

Purpose

Antiseptic, Alcohol wipes

Use

Daily cleaning

Warnings

1. This product is for external use, please do not put into mouth.
2. Not suitable for baby under 3 years old.
3. Normal temperture perservation, avoid sunlight irradiate.
4. Avoid directly touch with eyes. If accidentally get in your eyes, please wash with water immediately and seek medical attention.
5. If you got an anaphylactic reaction, stop using it immediately and consult to doctor.
6. Keep away from fire.

Not suitable for baby under 3 years old.

WHEN USING

Avoid directly touch with eyes. If accidentally get in your eyes, please wash with water immediately and seek medical attention.
If you got an anaphylactic reaction, stop using it immediately and consult to doctor.

STOP USE

If you got an anaphylactic reaction, stop using it immediately and consult to doctor.

KEEP OUT OF REACH OF CHILDREN

This product is for external use, please do not put into mouth.
Not suitable for baby under 3 years old.

Directions

1. Please lift off the sealing sticker on the top carefully, pull out the wipes from the opening.
2. After used, put the sealing sticker stick back to the opening to well keep the moisture of the wipes.

Other information

Normal temperture perservation, avoid sunlight irradiate.

Inactive ingredients

water

Package Label - Principal Display Panel

80 PCS NDC: 79288-001-01